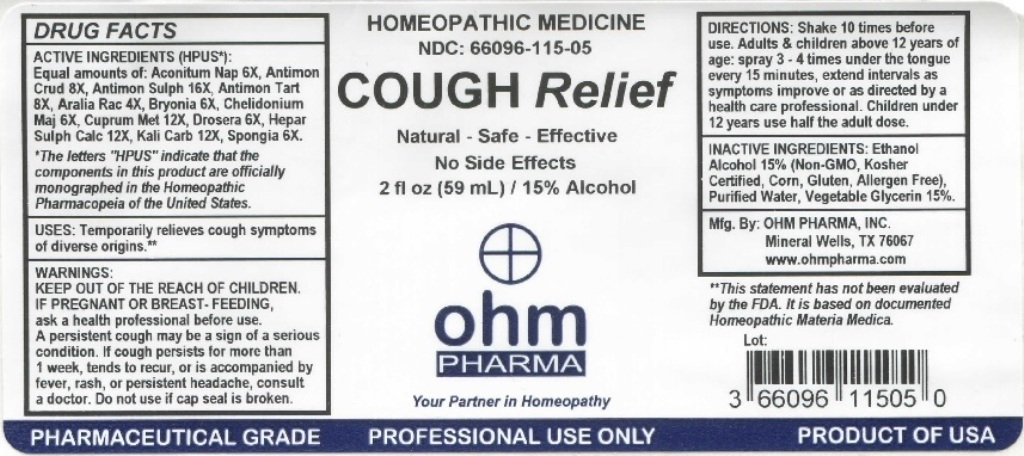 DRUG LABEL: Cough Relief
NDC: 66096-115 | Form: LIQUID
Manufacturer: OHM PHARMA INC.
Category: homeopathic | Type: HUMAN OTC DRUG LABEL
Date: 20211229

ACTIVE INGREDIENTS: ACONITUM NAPELLUS 6 [hp_X]/59 mL; ANTIMONY TRISULFIDE 8 [hp_X]/59 mL; ANTIMONY PENTASULFIDE 8 [hp_X]/59 mL; ANTIMONY POTASSIUM TARTRATE 8 [hp_X]/59 mL; ARALIA RACEMOSA ROOT 4 [hp_X]/59 mL; BRYONIA ALBA ROOT 6 [hp_X]/59 mL; CHELIDONIUM MAJUS 6 [hp_X]/59 mL; COPPER 12 [hp_X]/59 mL; DROSERA ROTUNDIFOLIA 6 [hp_X]/59 mL; CALCIUM SULFIDE 12 [hp_X]/59 mL; POTASSIUM CARBONATE 12 [hp_X]/59 mL; SPONGIA OFFICINALIS SKELETON, ROASTED 6 [hp_X]/59 mL
INACTIVE INGREDIENTS: ALCOHOL; WATER; GLYCERIN

OHM Cough Relief

ACTIVE INGREDIENT

ACTIVE INGREDIENTS (HPUS*): Equal amounts of: Aconitum Nap 6X, Antimon Crud 8X, Antimon Sulph 16X, Antimon Tart 8X, Aralia Rac 4X, Bryonia 6X, Chelidonium Maj 6X, Cuprum Met 12X, Drosera 6X, Hepar Sulph Calc 12X, Kali Carb 12X, Spongia 6X.

*The letters "HPUS" indicate that the components in this product are officially monographed in the Homeopathic Pharmacopeia of the United States.

INDICATIONS AND USAGE

USES: Temporarily relieves cough symptoms of diverse origins.

**This statement has not been evaluated by the FDA. It is based on documented Homeopathic Materia Medica.

WARNINGS

WARNINGS: IF PREGNANT OR BREAST-FEEDING, ask a health professional before use. If symptoms worsen or persist for more than a week, discontinue use and contact a doctor.

- KEEP OUT OF REACH OF CHILDREN.

DOSAGE AND ADMINISTRATION

DIRECTIONS: Shake 10 times before use. Adults & children above 12 years of age: spray 3-4 times under the tongue every 15 minutes, extend intervals as symptoms improve or as directed by a health care professional. Children under 12: use half the adult dose.

Do not use if cap seal is broken.

INACTIVE INGREDIENT

INACTIVE INGREDIENTS: Ethanol Alcohol 15% (Non-GMO, Kosher Certified, Corn, Gluten, Allergen Free), Purified Water, Vegetable Glycerin 15%.

QUESTIONS

Mfg. By: OHM PHARMA, INC. Mineral Wells, TX 76067

www.ohmpharma.com

PACKAGE LABEL

HOMEOPATHIC MEDICINE

NDC: 66096-115-05

COUGH Relief

Natural - Safe - Effective

No Side Effects

2 fl oz (59mL) / 15% Alcohol

PRODUCT OF USA

PURPOSE

Temporarily relieves cough.